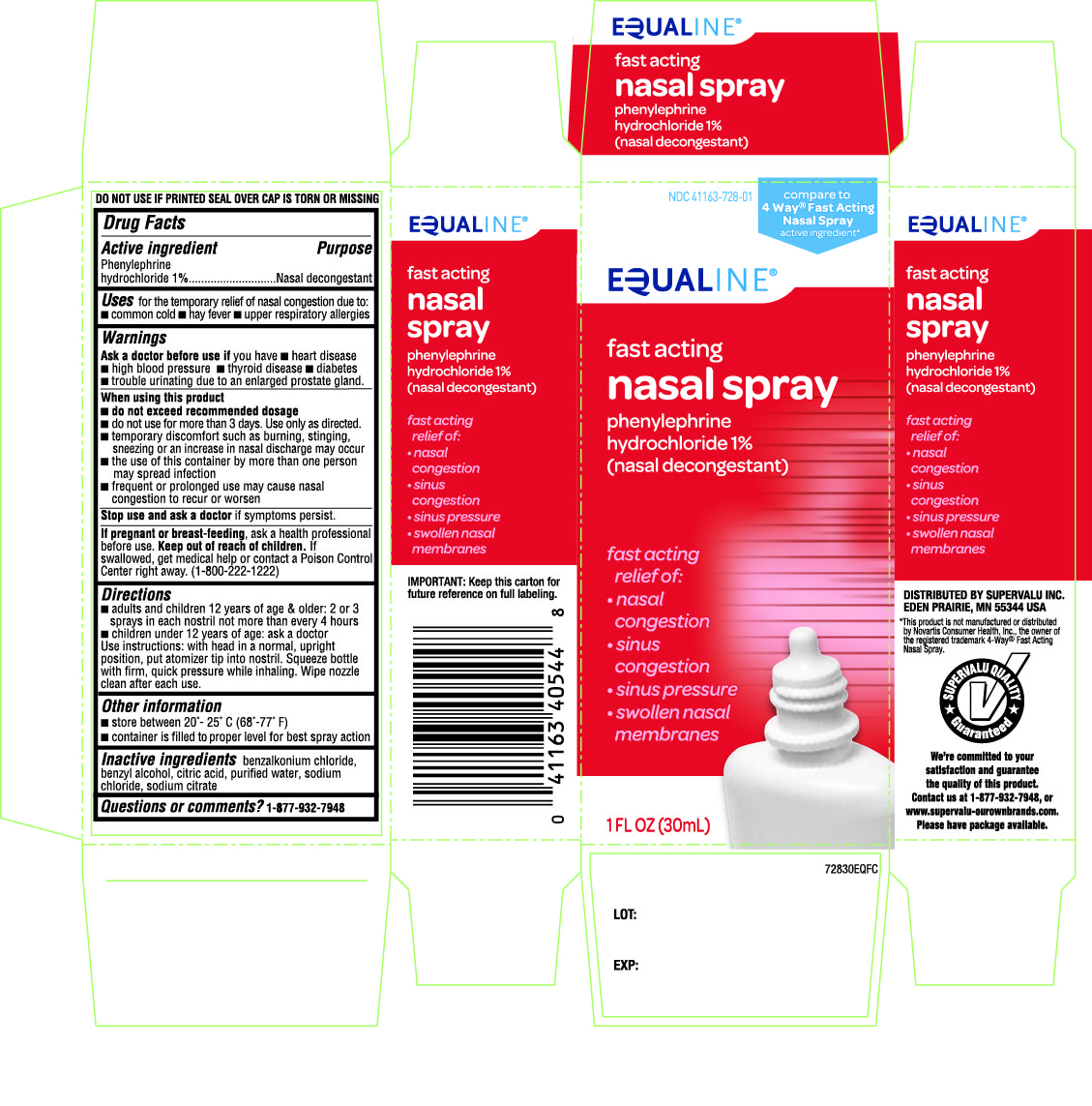 DRUG LABEL: Equaline
NDC: 41163-728 | Form: SPRAY
Manufacturer: SUPERVALU INC.
Category: otc | Type: HUMAN OTC DRUG LABEL
Date: 20141103

ACTIVE INGREDIENTS: PHENYLEPHRINE HYDROCHLORIDE 10 mg/1 mL
INACTIVE INGREDIENTS: BENZALKONIUM CHLORIDE; BENZYL ALCOHOL; CITRIC ACID MONOHYDRATE; WATER; SODIUM CHLORIDE; SODIUM CITRATE

Drug Facts

Active ingredient

Phenylephrine hydrochloride 1%

Purpose

Nasal decongestant

Uses

for the temporary relief of nasal congestion due to:

- common cold
- hay fever
- upper respiratory allergies

Ask a doctor before use if you have

- heart disease
- high blood pressure
- thyroid disease
- diabetes
- trouble urinating due to an enlarged prostate gland

When using this product

• do not exceed recommended dosage

• do not use for more than 3 days. Use only as directed

• temporary discomfort such as burning, stinging, sneezing, or an increase in nasal discharge may occur

• the use of this container by more than one person may spread infection

• frequent or prolonged use may cause nasal congestion to recur or worsen

Stop use and ask a doctor if

symptoms persist

If pregnant or breast-feeding

ask a health professional before use.

Keep out of reach of children

If swallowed, get medical help or contact a Poison Control Center right away (1-800-222-1222)

Directions

- adults and children 12 years of age and over: 2 or 3 sprays in each nostril not more than every 4 hours
- children under 12 years of age: ask a doctor
- Use instructions: with head in a normal, upright position, put atomizer tip into nostril. Squeeze bottle with firm, quick pressure while inhaling. Wipe nozzle clean after each use.

Other information

- store between 20°-25°C (68°-77°F)
- container is filled to proper level for best spray action

Inactive Ingredients

benzalkonium chloride, benzyl alcohol, citric acid, purified water, sodium chloride, sodium citrate

Questions

1-877-932-7948

IMPORTANT: Keep this carton for future reference on full labeling

DO NOT USE IF PRINTED SEAL OVER CAP IS TORN OR MISSING

Distributed By: Supervalu Inc.
Eden Prairie, MN 55344

This product is not manufactured or distributed by Novartis Consumer Health Inc., the owner of the registered trademark 4-Way Fast Acting Nasal Spray.

Principal Display

NDC 41163-728-01

Equaline

Fast Acting

Nasal Spray

Phenylephrine hydrochloride 1%

(nasal decongestant)

fast acting relief of

- nasal congestion
- sinus congestion
- sinus pressure
- swollen nasal passages

1 FL OZ (30mL)